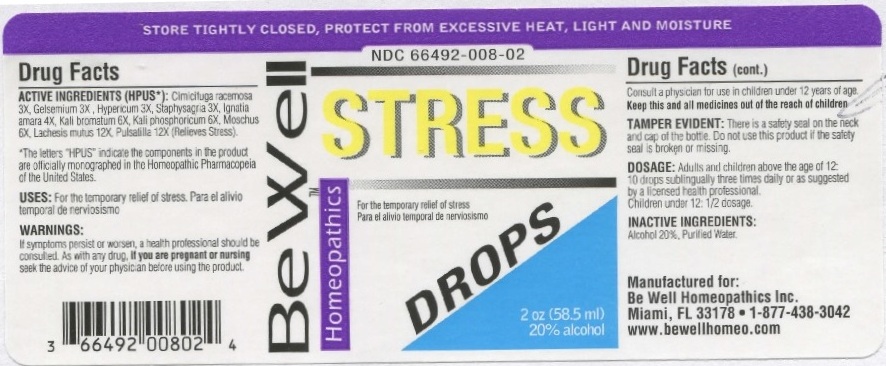 DRUG LABEL: Stress Drops
NDC: 66492-008 | Form: LIQUID
Manufacturer: Be Well Medical dba Richard Clement Nutrition y Be Well Homeopathics
Category: homeopathic | Type: HUMAN OTC DRUG LABEL
Date: 20211229

ACTIVE INGREDIENTS: BLACK COHOSH 3 [hp_X]/58.5 mL; GELSEMIUM SEMPERVIRENS ROOT 3 [hp_X]/58.5 mL; HYPERICUM PERFORATUM 3 [hp_X]/58.5 mL; DELPHINIUM STAPHISAGRIA SEED 3 [hp_X]/58.5 mL; STRYCHNOS IGNATII SEED 4 [hp_X]/58.5 mL; POTASSIUM BROMIDE 6 [hp_X]/58.5 mL; DIBASIC POTASSIUM PHOSPHATE 6 [hp_X]/58.5 mL; MOSCHUS MOSCHIFERUS MUSK SAC RESIN 6 [hp_X]/58.5 mL; LACHESIS MUTA VENOM 12 [hp_X]/58.5 mL; ANEMONE PULSATILLA 12 [hp_X]/58.5 mL
INACTIVE INGREDIENTS: ALCOHOL; WATER

Stress Drops

ACTIVE INGREDIENT

ACTIVE INGREDIENTS (HPUS*): Cimicifuga racemosa 3X, Gelsemium 3X, Hypericum3X, Staphysagria3X, Ignatia amara 4X, Kali bromatum 6X, Kali phosphoricum 6X, Moschus 6X, Lachesis mutus 12X, Pulsatilla 12X (Relieves Stress).

*The letters "HPUS" indicate that the components in the product are officially monographed in the Homeopathic Pharmacopeia of the United States.

INDICATIONS AND USAGE

USES: For the temporary relief of stress. Para el alivio temporal de nerviosismo

WARNINGS

WARNINGS: If symptoms persist or worsen, a health professional should be consulted. As with any drug, if you are pregnant or nursing seek the advice of your physician before using this product. Consult a physician for use in children under 12 years of age.

KEEP OUT OF REACH OF CHILDREN

Keep this and all medicines out of the reach of children.

DOSAGE AND ADMINISTRATION

DOSAGE: Adults and children above the age of 12: 10 drops sublingually three times daily or as suggested by a licensed health professional. Children under 12: 1/2 dosage.

OTHER SAFETY INFORMATION

TAMPER EVIDENT: There is a safety seal on the neck and cap of the bottle. Do not use this product if the safety seal is broken or missing.

INACTIVE INGREDIENTS: Alcohol 20%, Purified Water.

QUESTIONS

Manufactured for: Be Well Homeopathics Inc. Miami, FL 33178 • 1-877-438-3042

www.bewellhomeo.com

PACKAGE LABEL

STORE TIGHTLY CLOSED, PROTECT FROM EXCESSIVE HEAT, LIGHT AND MOISTURE

NDC 66492-008-02

Homeopathics

Be Well STRESS Drops

For the temporary relief of stress. Para el alivio temporal de nerviosismo

2oz (58.5 ml)

20% alcohol

PURPOSE

For the temporary relief of stress. Para el alivio temporal de nerviosismo